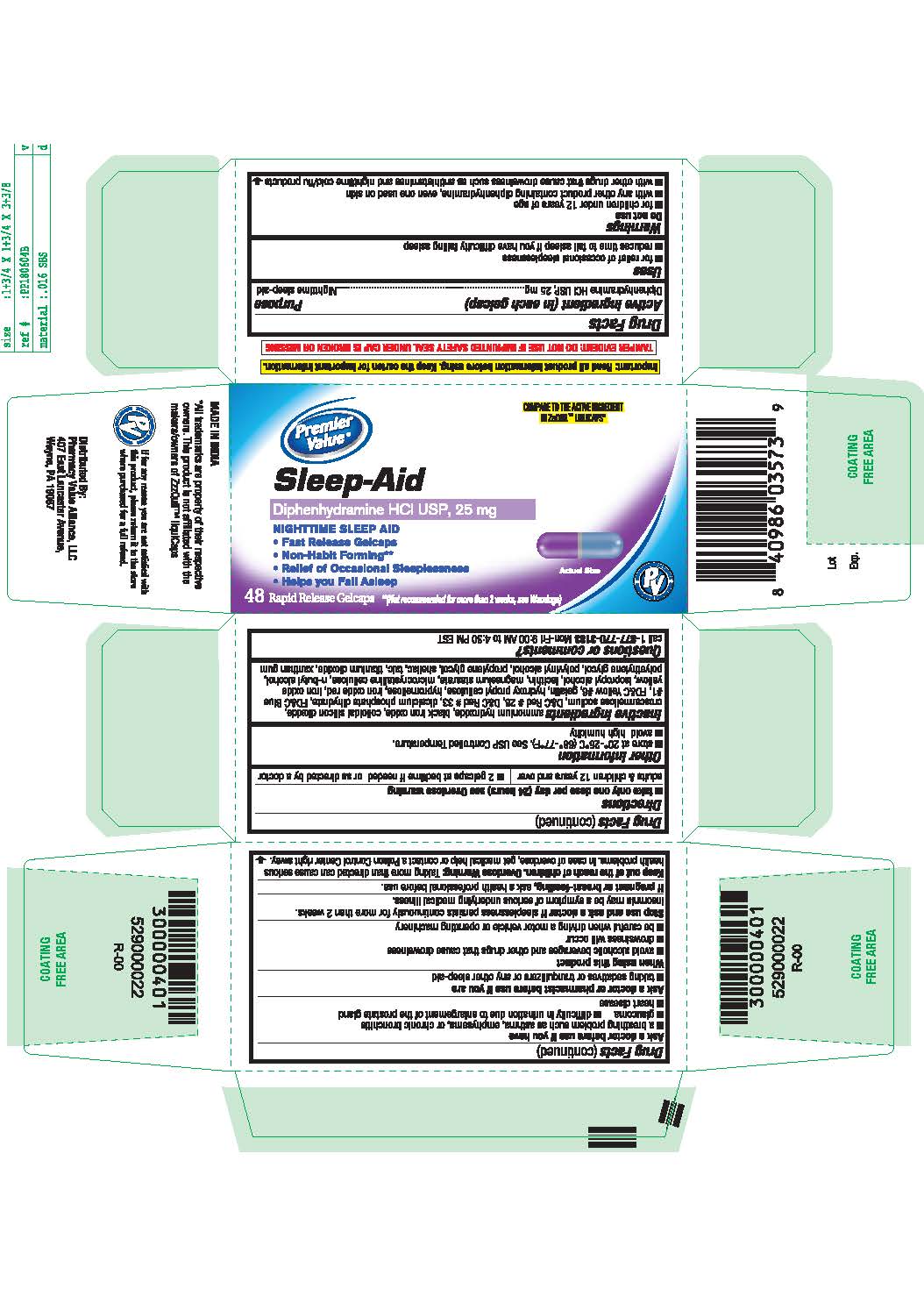 DRUG LABEL: Diphenhydramine Hydrochloride
NDC: 68016-789 | Form: TABLET
Manufacturer: Pharmacy Value Alliance, LLC
Category: otc | Type: HUMAN OTC DRUG LABEL
Date: 20210129

ACTIVE INGREDIENTS: DIPHENHYDRAMINE HYDROCHLORIDE 25 mg/1 1
INACTIVE INGREDIENTS: D&C RED NO. 33; AMMONIA; DIBASIC CALCIUM PHOSPHATE DIHYDRATE; FD&C YELLOW NO. 6; FERRIC OXIDE RED; MAGNESIUM STEARATE; BUTYL ALCOHOL; SHELLAC; XANTHAN GUM; POLYETHYLENE GLYCOL, UNSPECIFIED; POLYVINYL ALCOHOL, UNSPECIFIED; TALC; FD&C BLUE NO. 1; GELATIN; HYDROXYPROPYL CELLULOSE, UNSPECIFIED; HYPROMELLOSES; FERRIC OXIDE YELLOW; SILICON DIOXIDE; CROSCARMELLOSE SODIUM; D&C RED NO. 28; FERROSOFERRIC OXIDE; ISOPROPYL ALCOHOL; LECITHIN, SOYBEAN; CELLULOSE, MICROCRYSTALLINE; PROPYLENE GLYCOL; TITANIUM DIOXIDE

Sleep-Aid
Diphenhydramine HCl USP, 25 mg
NIGHTTIME SLEEP AID

Active ingredient

(in each gelcap)

Diphenhydramine HCl USP, 25 mg

Purpose

Nighttime sleep-aid

Uses

■ for relief of occasional sleeplessness

■ reduces time to fall asleep if you have difficulty falling asleep.

Do not use

■ for children under 12 years of age

■ with any other product containing diphenhydramine, even one used on skin

■ with other drugs that cause drowsiness such as antihistamines and nighttime cold/flu products

Ask a doctor before use if you have

■ a breathing problem such as asthma, emphysema, or chronic bronchitis

■ glaucoma

■ difficulty in urination due to enlargement of the prostate gland

■ heart disease

Ask a doctor or pharmacist before use if you are

■ taking sedatives or tranquilizers or any other sleep-aid

When using this product

■ avoid alcoholic beverages and other drugs that cause drowsiness

■ drowsiness will occur

■ be careful when driving a motor vehicle or operating machinery

Stop use and ask a doctor if

sleeplessness persists continuously for more than 2 weeks. Insomnia may be a symptom of serious underlying medical illness.

If pregnant or breast-feeding,

ask a health professional before use.

Keep out of reach of children

Overdose Warning:

Taking more than directed can cause serious health problems. In case of overdose, get medical help or contact a Poison Control Center right away.

Directions

take only one dose per day (24 hours) see Overdose warning

adults & children 12 years and over

2 gelcaps at bedtime if needed or as directed by a doctor

Other information

■ store at 20°-25°C (68°-77°F). See USP Controlled Temperature.

■ avoid high humidity

Inactive ingredients

ammonium hydroxide, black iron oxide, colloidal silicon dioxide, croscarmellose sodium, D&C red # 28, D&C red # 33, dicalcium phosphate dihydrate, FD&C blue #1, FD&C yellow #6 gelatin, hydroxyl propyl cellulose, hypromellose, iron oxide red, iron oxide yellow, isopropyl alcohol, lecithin, magnesium stearate, microcrystalline cellulose, n-butyl alcohol, polyethylene glycol, polyvinyl alcohol, propylene glycol, shellac, talc, titanium dioxide, xanthan gum

Questions or comments?

call 1-877-770-3183 Mon-Fri 9:00 AM to 4:30 PM EST.